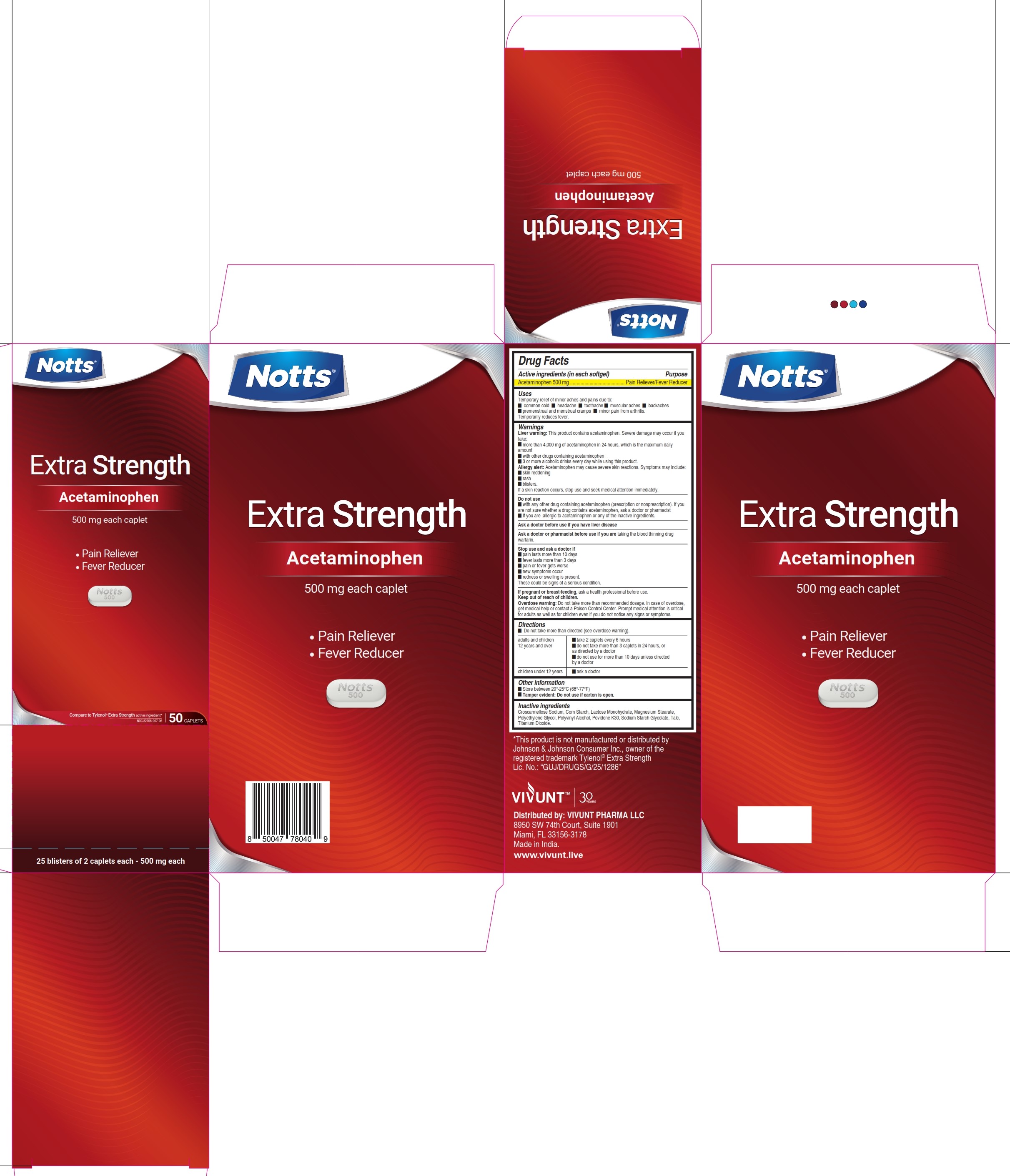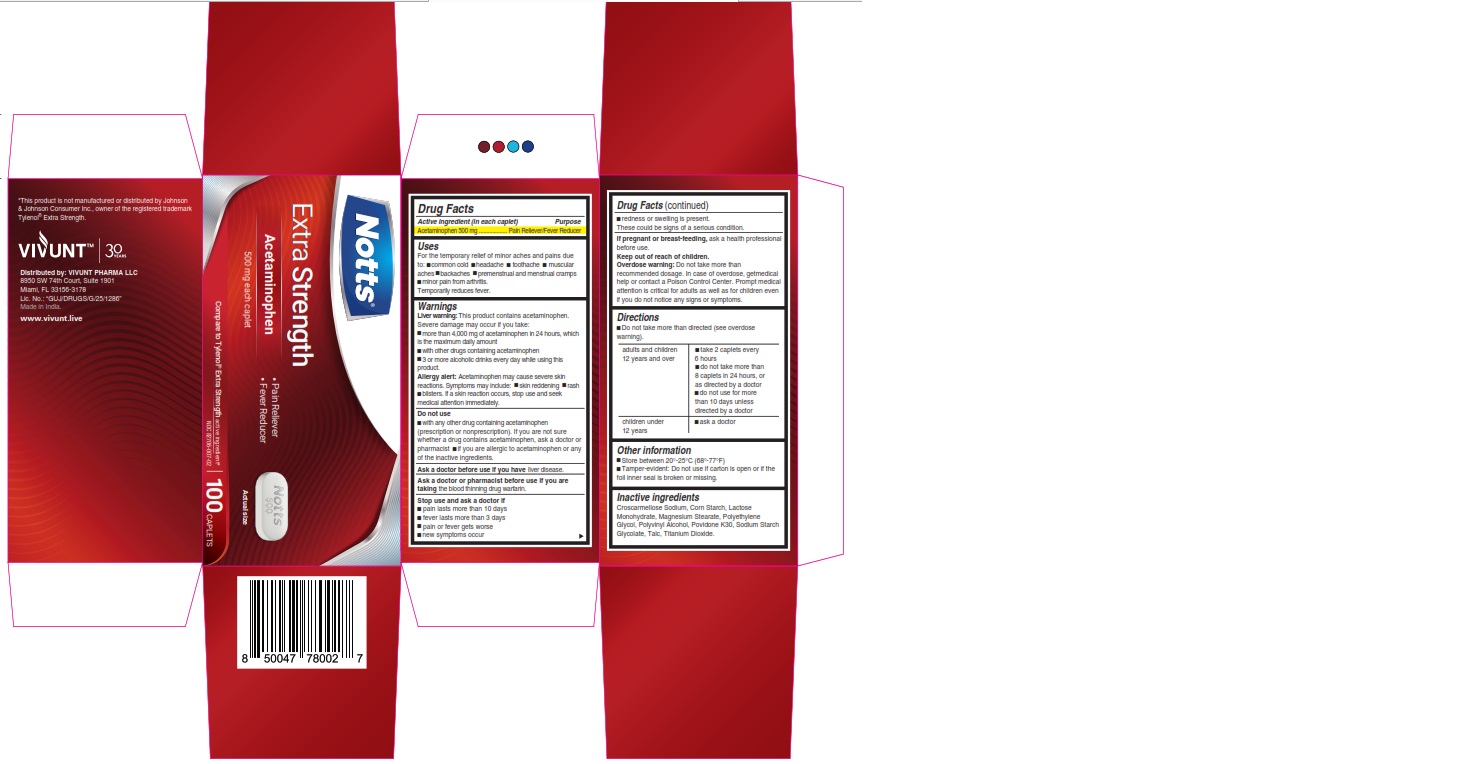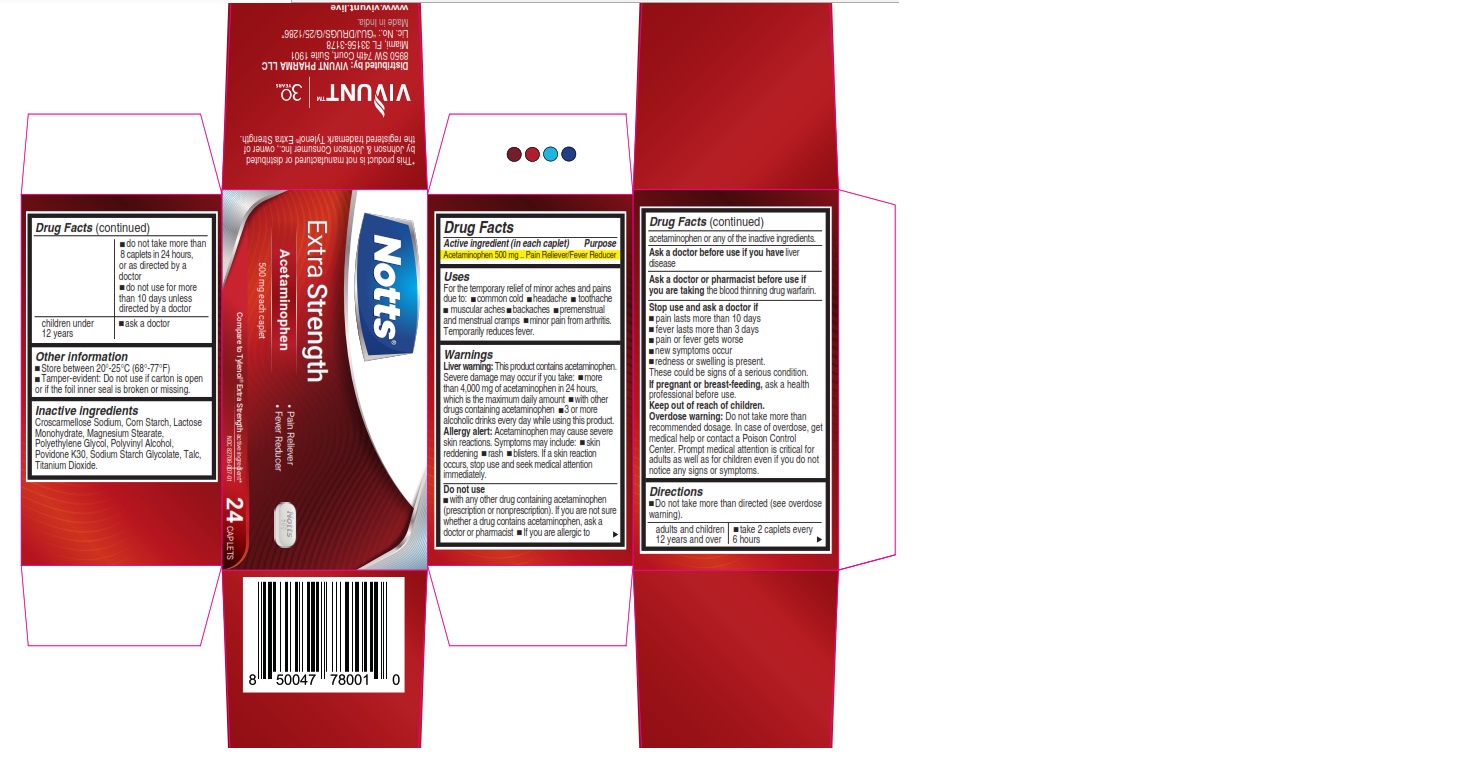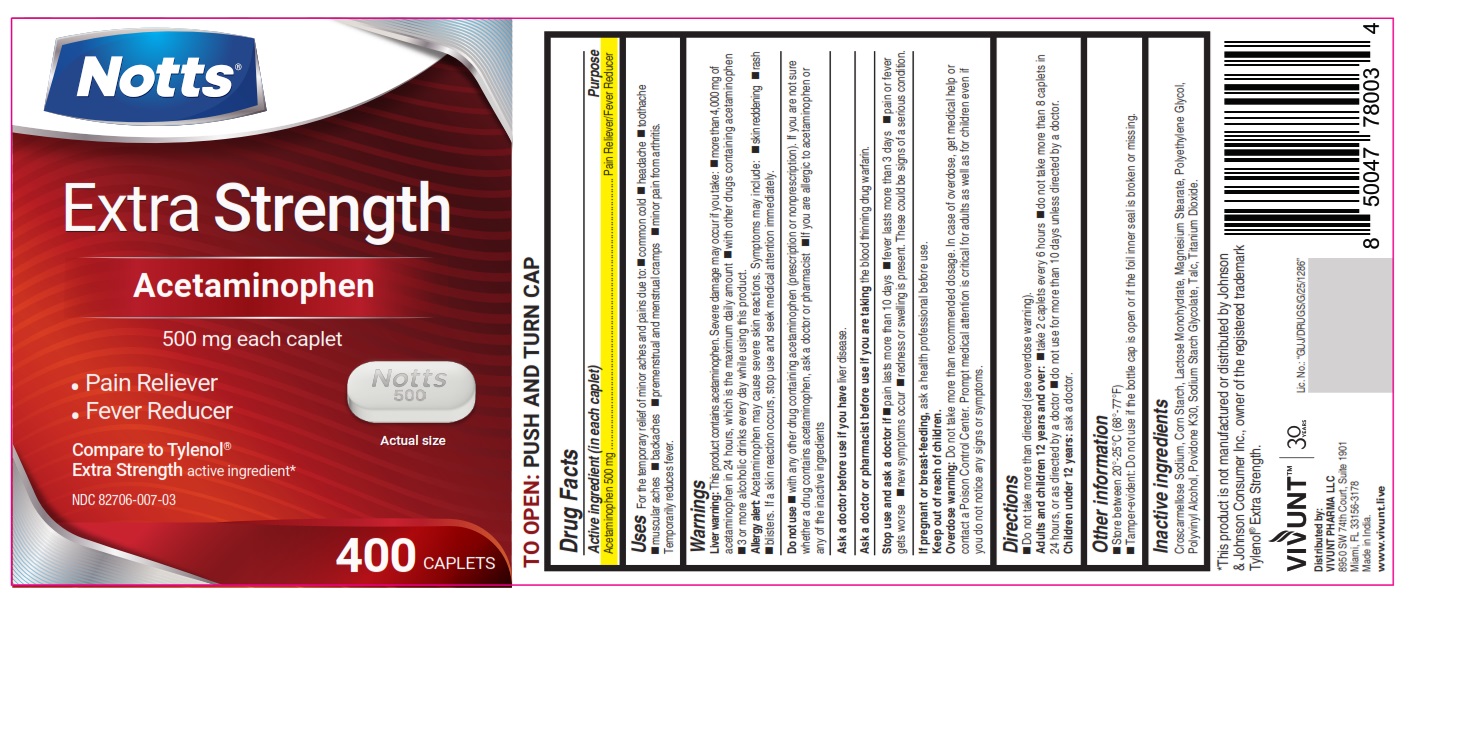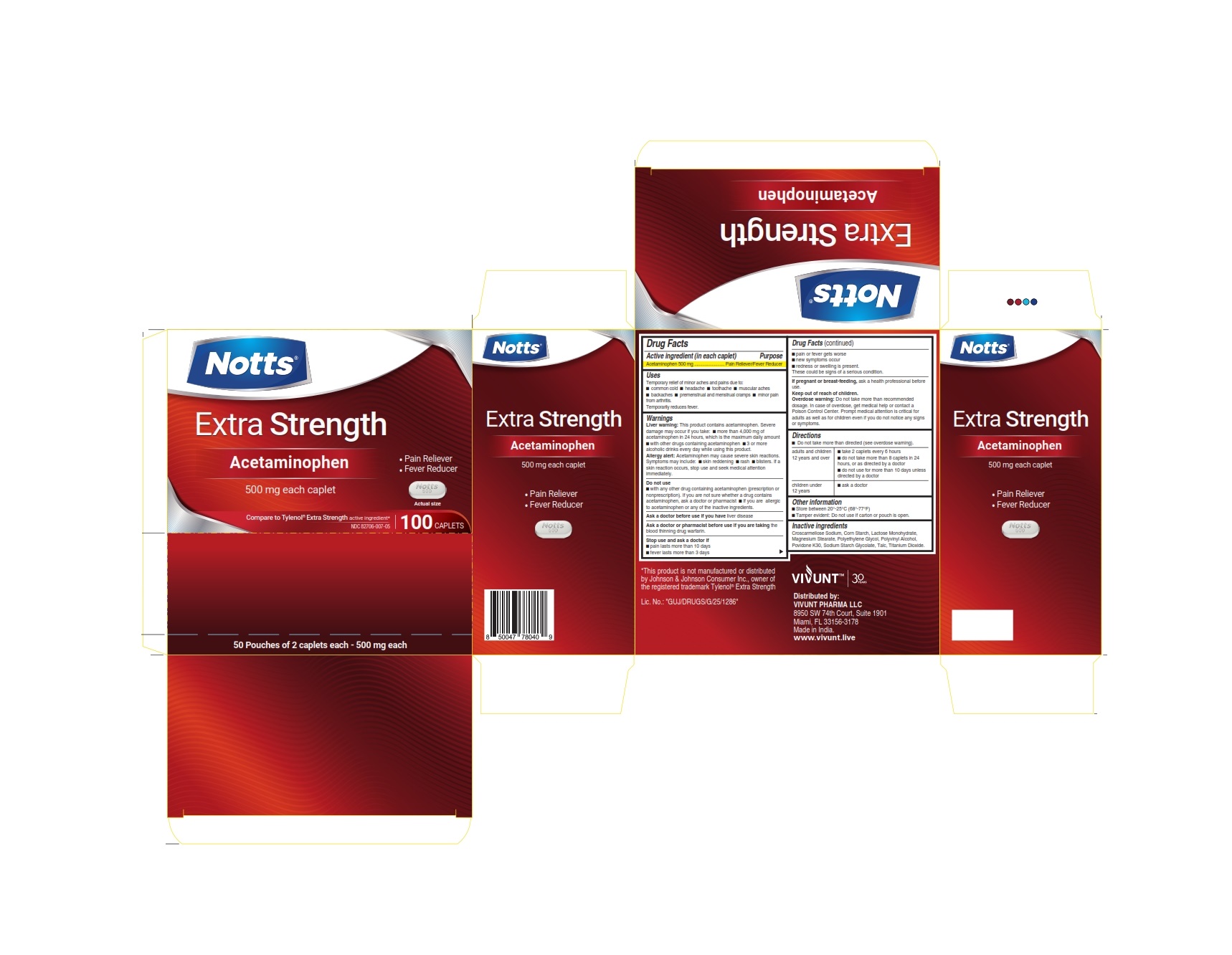 DRUG LABEL: NOTTS - Extra Strength 500 mg
NDC: 82706-007 | Form: TABLET
Manufacturer: VIVUNT PHARMA LLC
Category: otc | Type: HUMAN OTC DRUG LABEL
Date: 20250212

ACTIVE INGREDIENTS: ACETAMINOPHEN 500 mg/1 1
INACTIVE INGREDIENTS: POLYVINYL ALCOHOL, UNSPECIFIED; MAGNESIUM STEARATE; POLYETHYLENE GLYCOL, UNSPECIFIED; MICROCRYSTALLINE CELLULOSE; LECITHIN, SOYBEAN; SODIUM STARCH GLYCOLATE TYPE A; TITANIUM DIOXIDE; TALC; POVIDONE; STEARIC ACID; STARCH, CORN

NOTTS - Extra Strength 500 mg

Drug Facts

ACTIVE INGREDIENT

Active ingredient (in each caplet) | Purpose
Acetaminophen 500 mg | Pain Reliever/Fever Reducer

Uses

Temporary relief of minor aches and pains due to:

● common cold
● headache
● toothache
● muscular aches
● backaches
● premenstrual and menstrual cramps
● minor pain from arthritis

Temporarily reduces fever

Warnings

Liver Warning

This product contains acetaminophen. Severe liver damage may occur if you take:

- more than 4,000 mg of acetaminophen in 24 hours, which is the maximum daily amount.
- with other drugs containing acetaminophen.
- 3 or more alcoholic drinks every day while using this product.

Allergy Alert

Acetaminophen may cause severe skin reactions. Symptoms may include:

- skin reddening
- rash
- blisters

If a skin reaction occurs, stop use and seek medical attention immediately.

Do not use

- with any other drug containing acetaminophen (prescription or nonprescription). If you are not sure whether a drug contains acetaminophen, ask a doctor or pharmacist.
- if you are allergic to acetaminophen or any of the inactive ingredients.

Ask a doctor before use if you have

liver disease

Ask a doctor or pharmacist before use if you are taking

the blood thinning drug warfarin

Stop use and ask a doctor if

- pain lasts more than 10 days
- fever lasts more than 3 days
- pain or fever gets worse
- new symptoms occur
- redness or swelling is present

These could be signs of a serious condition.

If pregnant or breast-feeding,

ask a health professional before use.

Keep out of reach of children.

Overdose warning

Do not take more than recommended dosage. In case of overdose, get medical help or contact a Poison Control Center. Prompt medical attention is critical for adults as well as for children even if you do not notice any signs or symptoms.

Directions

- Do not take more than directed (see overdose warning)

adults and children 12 years and over | - take 2 caplets every 6 hours - do not take more than 8 caplets in 24 hours, or as directed by a doctor - do not use for more than 10 days unless directed by a doctor
children under 12 years | ask a doctor

Other information

- Store between 20-25°C (68-77°F)
- Tamper-evident: Do not use if carton is open or if the foil inner seal is broken or missing.
- Tamper-evident: Do not use if the bottle cap is open or if the foil inner seal is broken or missing.

Inactive ingredients

Croscarmellose Sodium, Corn Starch, Lactose Monohydrate, Magnesium Stearate, Polyethylene Glycol, Polyvinyl Alcohol, Povidone K30, Sodium Starch Glycolate, Talc, Titanium Dioxide.

*This product is not manufactured or distributed by Johnson & Johnson Consumer Inc., owner of the registered trademark Tylenol®Extra Strength.

Distributed by:

VIVUNT PHARMA LLC

8950 SW 74th Court, Suite 1901

Miami, FL 33156-3178

Made in India

PRINCIPAL DISPLAY PANEL - 24 Caplets

NOTTS™

Extra Strength

Acetaminophen

- Pain Reliever
- Fever Reducer

Compare to Tylenol® Extra Strength active ingredients*

NDC 82706-007-01

500 mg each caplet

24 CAPLETS

Extra Strength.

PRINCIPAL DISPLAY PANEL - 100 Caplets

NOTTS™

Extra Strength

Acetaminophen

- Pain Reliever
- Fever Reducer

Compare to Tylenol® Extra Strength active ingredients*

NDC 82706-007-02

500 mg each caplet

100 CAPLETS

Extra Strength.

PRINCIPAL DISPLAY PANEL - 400 Caplets

NOTTS™

Extra Strength

Acetaminophen

- Pain Reliever
- Fever Reducer

NDC 82706-007-03

500 mg each caplet

400 CAPLETS

Extra Strength.

PRINCIPAL DISPLAY PANEL 2 - 100 Caplets

NOTTS™

Extra Strength

Acetaminophen

Pain Reliever
Fever Reducer

Compare to Tylenol® Extra Strength active ingredients*

NDC 82706-007-05

500 mg each caplet

100 CAPLETS

Extra Strength.

50 pouches of 2 caplets each

500 mg each

Principal display 50 caplets

NOTTS™

Extra Strength

Acetaminophen

Pain Reliever
Fever Reducer

Compare to Tylenol® Extra Strength active ingredients*

NDC 82706-007-06

500 mg each caplet

50 CAPLETS

Extra Strength.

25 blisters of 2 caplets each

500 mg each